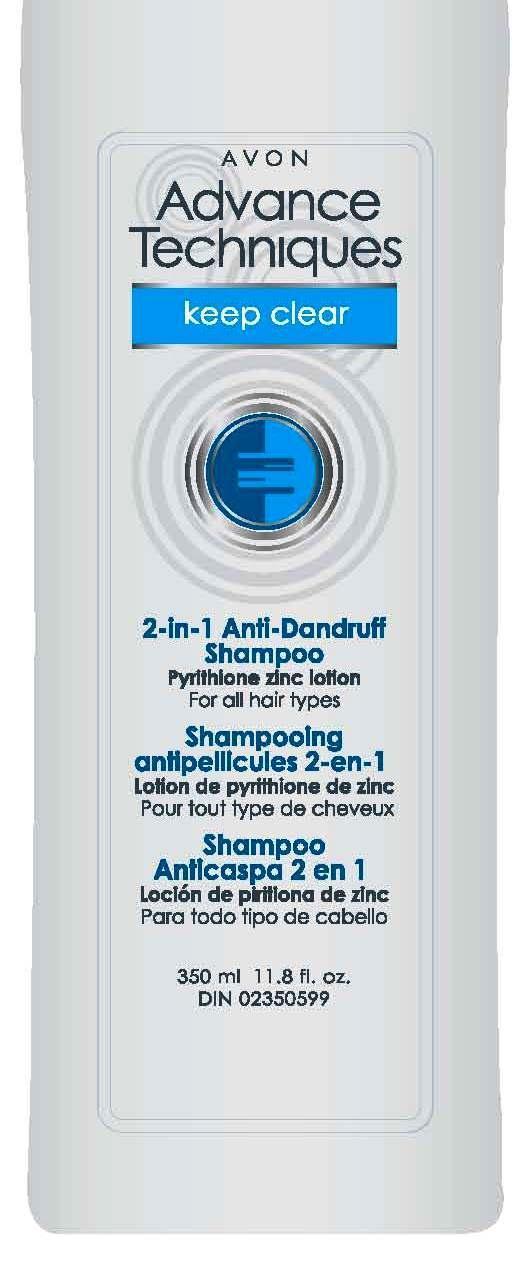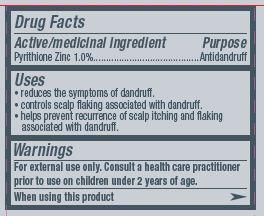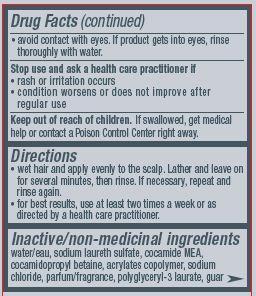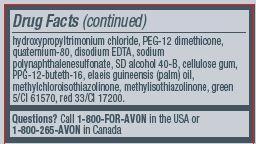 DRUG LABEL: Advance Techniques Keep Clear
NDC: 10096-0221 | Form: SHAMPOO
Manufacturer: Avon Products, Inc.
Category: otc | Type: HUMAN OTC DRUG LABEL
Date: 20130926

ACTIVE INGREDIENTS: PYRITHIONE ZINC 10 mg/1 mL

Active/medicinal ingredient
Pyrithione Zinc 1.0%.........................

Purpose

...................Antidandruff

Uses

- reduces the symptoms of dandruff
- controls scalp flaking associated with dandruff
- helps prevent recurrence of scalp itching and flaking associated with dandruff.

Warnings
For external use only. Consult a health care practitioner prior to use in children under 2 years of age.

When using this product

- avoid contact with eyes. If product gets into eyes, rinse thoroughly with water.

ASK DOCTOR

Stop us and ask a health care practitioner if

- rash or irritation occurs
- condition worsens or does not improve after regular use.

Keep out of reach of children. If swallowed, get medical help or contact a Poison Control Center right away.

Directions

- wet hair and apply evenly to the scalp. Lather and leave on for several minutes, then rinse. If necessary, repeat and rinse again.
- for best results, use at least two times a week or as directed by a health care practitioner.

Inactive/non-medicinal ingredients:

water/eau, sodium laureth sulfate, cocamide MEA, cocamidopropyl betaine, acrylates copolymer, sodium chloride, parfum/fragrance, polyglyceryl-3 laurate, guar hydroxypropyltrimonium chloride, PEG-12 dimethicone, quaternium-80, disodium EDTA, sodium polynaphthalenesulfonate, SD alcohol 40-B, cellulose gum, PPG-12-buteth-16, elaeis guineensis (palm) oil, methylchloroisothiazolinone, methylisothiazolinone, green 5/CI 61570, red 33/CI 17200.

QUESTIONS

Questions? Call 1-800-FOR-AVON or 1-800-265-AVON in Canada